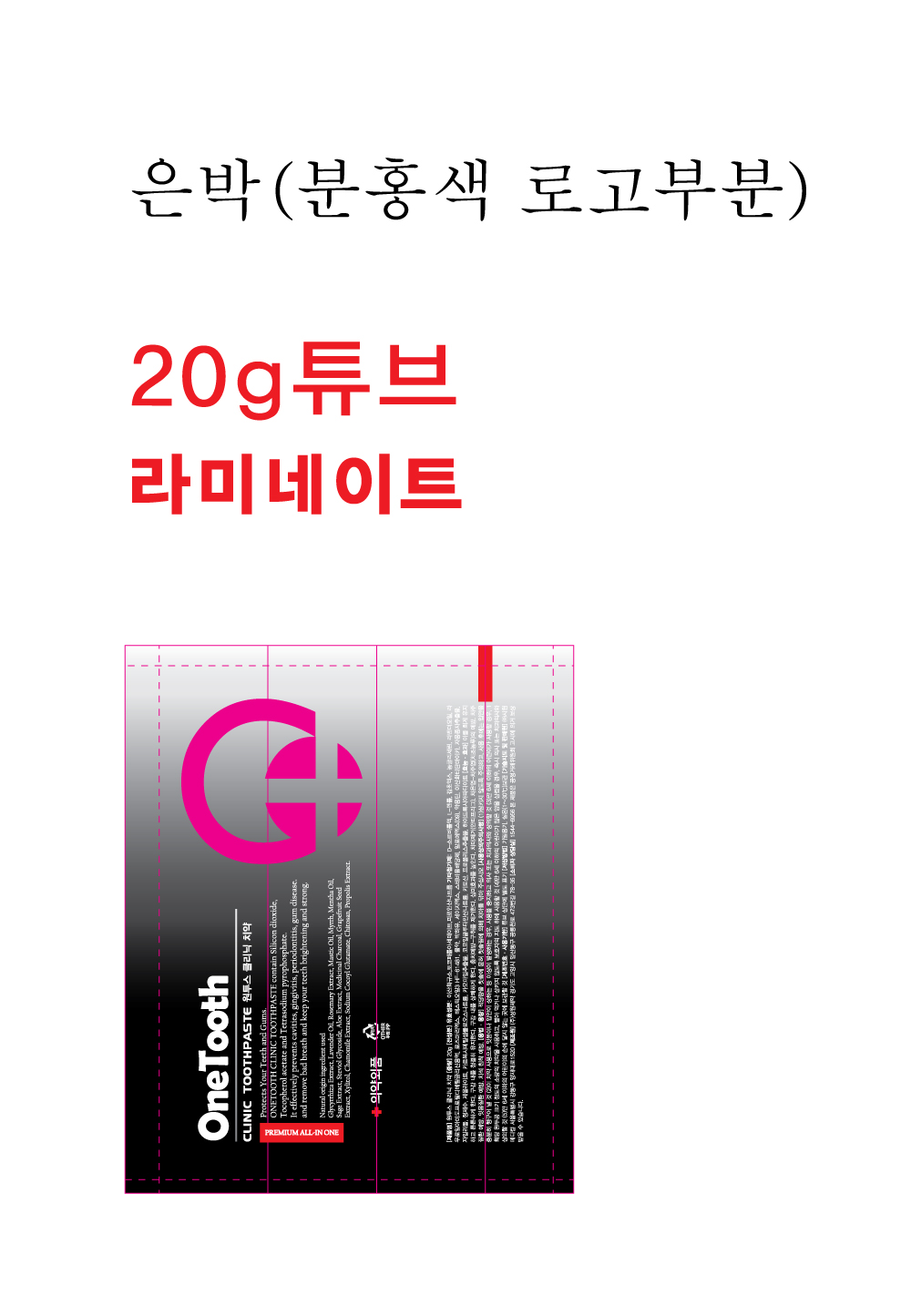 DRUG LABEL: ONETOOTH CLINIC TOOTH
NDC: 73527-0002 | Form: PASTE
Manufacturer: CONE MEDICAL Co., Ltd.
Category: otc | Type: HUMAN OTC DRUG LABEL
Date: 20251230

ACTIVE INGREDIENTS: SODIUM PYROPHOSPHATE 0.5 g/100 g; SILICON DIOXIDE 14 g/100 g; ALPHA-TOCOPHEROL ACETATE 0.1 g/100 g
INACTIVE INGREDIENTS: XYLITOL; WATER; SORBITOL

ACTIVE INGREDIENT

Silicon Dioxide, Tocopherol Acetate, Tetrasodium Pyrophosphate

PURPOSE

For dental health

For dental care

Keep out of reach of children

INDICATIONS AND USAGE

Brushing the teeth with a suitable amount

WARNINGS

- Do not swallow and rinse mouth thoroughly after use
- If you experience any problems with your gums or mouth during use, discontinue use and consult your doctor.
- For children under 6 years of age, use small amounts of toothpaste. And
- use itunder the supervision of a guardian to avoid sucking or swallowing.
- Consult a physician or dentist immediately if a child under 6 years old
- hasswallowed large quantities.
- Keep out of the reach of children under 6 years of age.

INACTIVE INGREDIENT

D-Sorbitol Solution, Concentrated Glycerin, Carboxymethylcellulose Sodium, Hydroxyapatite, Medicinal Carbon, Chitosan, Titanium Oxide and Mica, Zeolite, Xylitol, Steviol Glycoside, Papain, Grapefruit Seed Extract, L-Menthol, Mentha Oil, Propolis Extract, Chamomile Extract, Rosemary Extract, Sage Extract, Aloe Extract, Glycyrrhiza Extract, Lavender Oil, Horsetail Extract, Sodium Cocoyl Glutamate, Lauroyl Amidopropyl Dimethyl Glycine Solution, Deionized Water

DOSAGE AND ADMINISTRATION

For dental use only